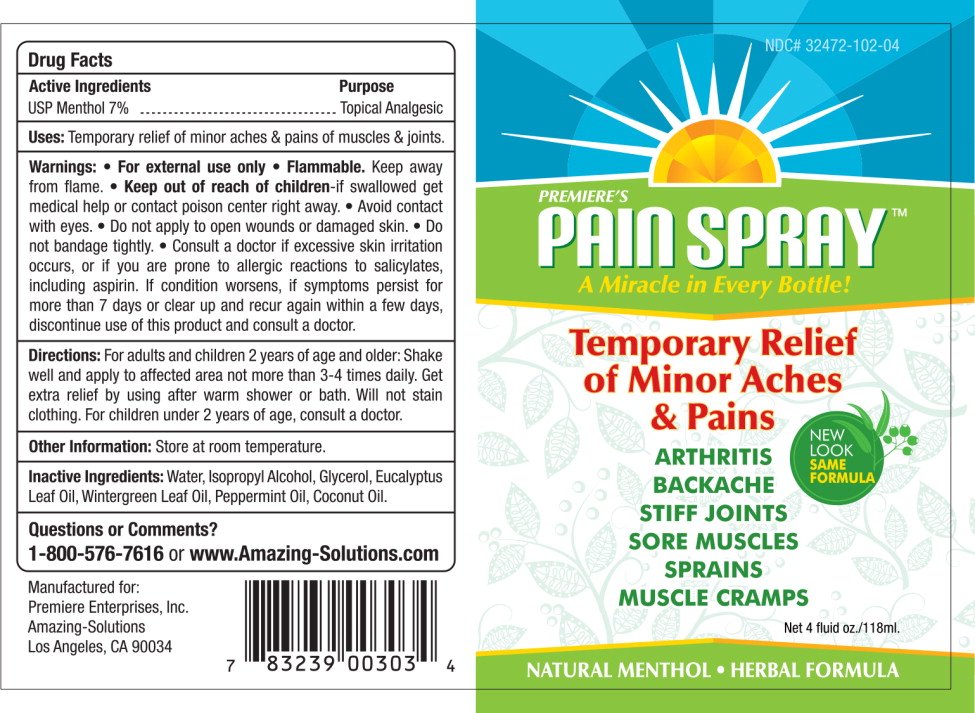 DRUG LABEL: PREMIERES PAIN
NDC: 32472-102 | Form: SPRAY
Manufacturer: Premiere Enterprises
Category: otc | Type: HUMAN OTC DRUG LABEL
Date: 20251223

ACTIVE INGREDIENTS: MENTHOL 0.07 g/1 mL
INACTIVE INGREDIENTS: WATER; ISOPROPYL ALCOHOL; GLYCERIN; EUCALYPTUS OIL; METHYL SALICYLATE; PEPPERMINT OIL; COCONUT OIL

PREMIERE'S PAIN SPRAY

Premiere Enterprises, Inc.

Pain Spray

Drug Facts

Active Ingredients

USP Menthol 7%

Purpose

Topical Analgesic

Uses:

For the temporary relief of minor aches and pains of muscles and joints.

Warnings:

- For external use only
- Flammable.Keep away from flame.

- Keep out of reach of children-if swallowed get medical help or contact a poison center right away.
- Avoid contact with eyes
- Do not apply to open wounds or damaged skin
- Do not bandage tightly
- Consult a doctor if excessive skin irritation occurs, or if you are prone to allergic reactions to salicylates, including aspirin. If condition worsens, if symptoms persist for more than 7 days or clear up and recur again within a few days, discontinue use of this product and consult a doctor.

Directions:

For adults and children 2 years of age and older: Shake well and apply to affected area not more than 3-4 times daily. Get extra relief by using after warm shower or bath. Will not stain clothing. For children under 2 years of age, consult a Doctor.

Other Information:

Store at room temperature.

Inactive Ingredients:

Water, Isopropyl Alcohol, Glycerol, Eucalyptus Leaf Oil, Wintergreen Leaf Oil, Peppermint Oil, Coconut Oil.

Questions or Comments?

1-800-576-7616or www.Amazing-Solutions.com

Manufactured for:
PREMIERE ENTERPRISES, INC.
Los Angeles, CA 90034

PRINCIPAL DISPLAY PANEL

NDC# 32472-102-04

PREMIERE'S

Pain Spray™

A Miracle in Every Bottle!

Temporary Relief
of Minor Aches
& Pains

NEW LOOK
SAME FORMULA

ARTHRITIS
BACKACHE
STIFF JOINTS
SORE MUSCLES
SPRAINS
MUSCLE CRAMPS

Net 4 fluid oz./118 ml.

NATURAL MENTHOL • HERBAL FORMULA